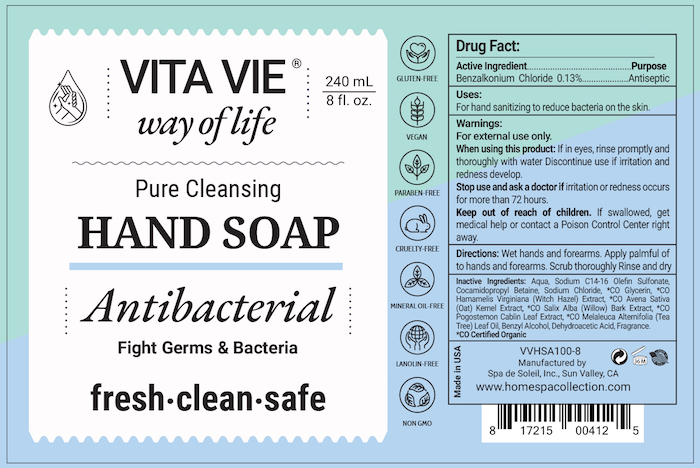 DRUG LABEL: VitaVie
NDC: 68062-2219 | Form: SOLUTION
Manufacturer: Spa De Soleil
Category: otc | Type: HUMAN OTC DRUG LABEL
Date: 20260121

ACTIVE INGREDIENTS: BENZALKONIUM CHLORIDE 0.312 g/240 mL
INACTIVE INGREDIENTS: WATER; GLYCERIN

Vita Vie

Active Ingredient - Benzalkonium Chloride 0.13%

Purpose - Antispetic Handwash

PURPOSE

Uses - For handwashing to decrease bacteria on the skin

Warnings - For external use only

When using this product avoid contact with eyes. In case of eye contact, rinse promptly and thoroughly with water.

Stop use and ask a doctor if irritation and redness occurs for more than 72 hours.

Keep out of reach of children. If swallowed, get medical help or contact a Poison Control Center right away.

INDICATIONS AND USAGE

Directions: We hands and forearms. Apply a palmful of foam to hands and lather over hands and forearms. Scrub thoroughly. Rinse and dry.

DOSAGE AND ADMINISTRATION

Repeat applications as needed.

INACTIVE INGREDIENT

Inactive Ingredients: Aqua, Sodium C14-16 Olefin Sulfonate, Cocamidopropyl Betaine, Sodium Chloride, *CO Glycerin, *CO Hamamelis Virginiana (Witch Hazel) Extract, *CO Avena Sativa (Oat) Kernel Extract, *CO Salix Alba (Willow) Bark Extract, *CO Pogostemon Cablin Leaf Extract, *CO Melaleuca Alternifolia (Tea Tree) Leaf Oil, Benzyl Alcohol, Dehydroacetic Acid, Fragrance.

*CO Certified Organic